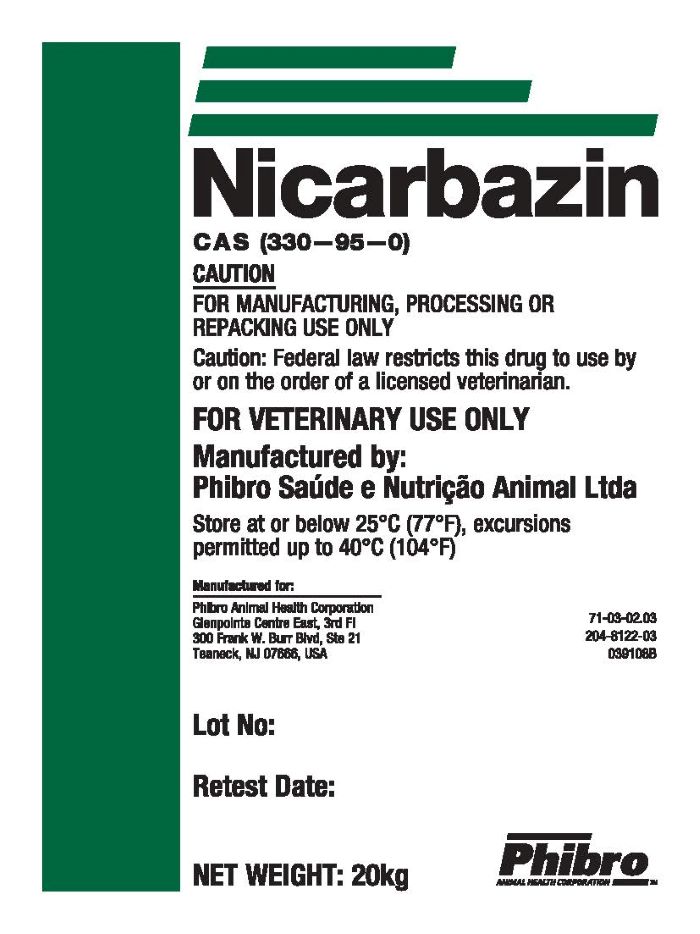 DRUG LABEL: Nicarbazin
NDC: 66104-9078 | Form: POWDER
Manufacturer: Phibro Animal Health
Category: other | Type: BULK INGREDIENT - ANIMAL DRUG
Date: 20250327

ACTIVE INGREDIENTS: NICARBAZIN 1 kg/1 kg

Nicarbazin

CAS (330-95-0)

CAUTION:

FOR MANUFACTURING, PROCESSING OR REPACKING USE ONLY

Caution: Federal law restricts this drug to use by or on the order of a licensed veterinarian.

FOR VETERINARY USE ONLY

Manufactured by:

Phibro Saude e Nutricao Animal Ltda

Net Weight: 20 KG

Manufactured for:

Phibro Animal Health Corporation

GlenPointe Centre East, 3rd Floor

300 Frank W. Burr Blvd, Ste 21

Teaneck , NJ 07666, USA

STORAGE AND HANDLING

Store at or below 25°C (77°F), excursions permitted up to 40°C (104°F)